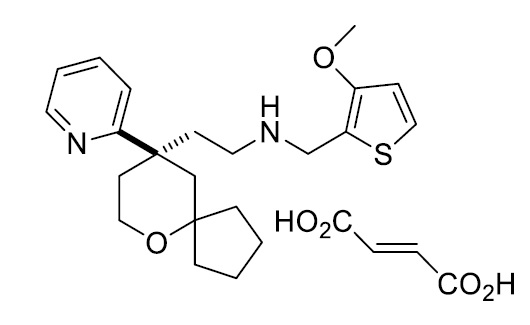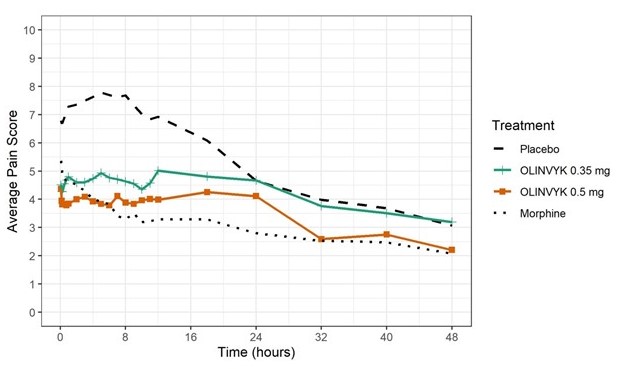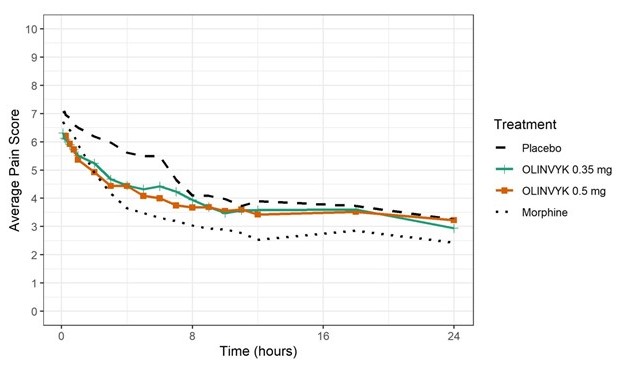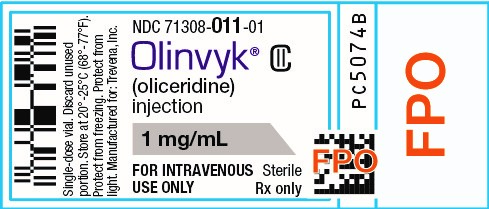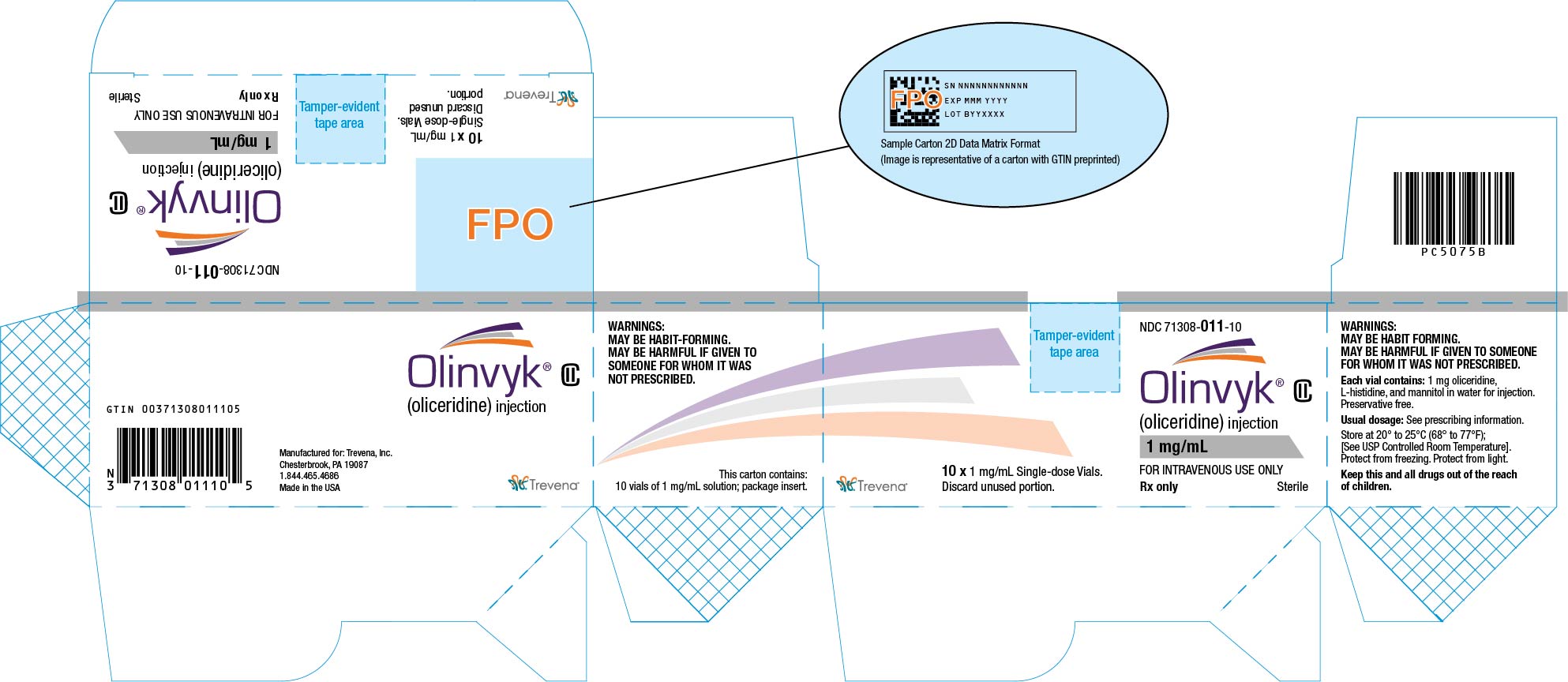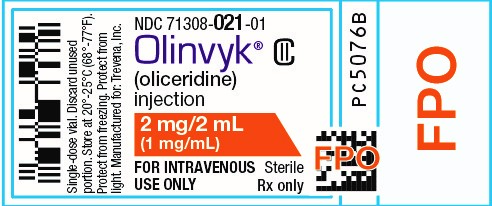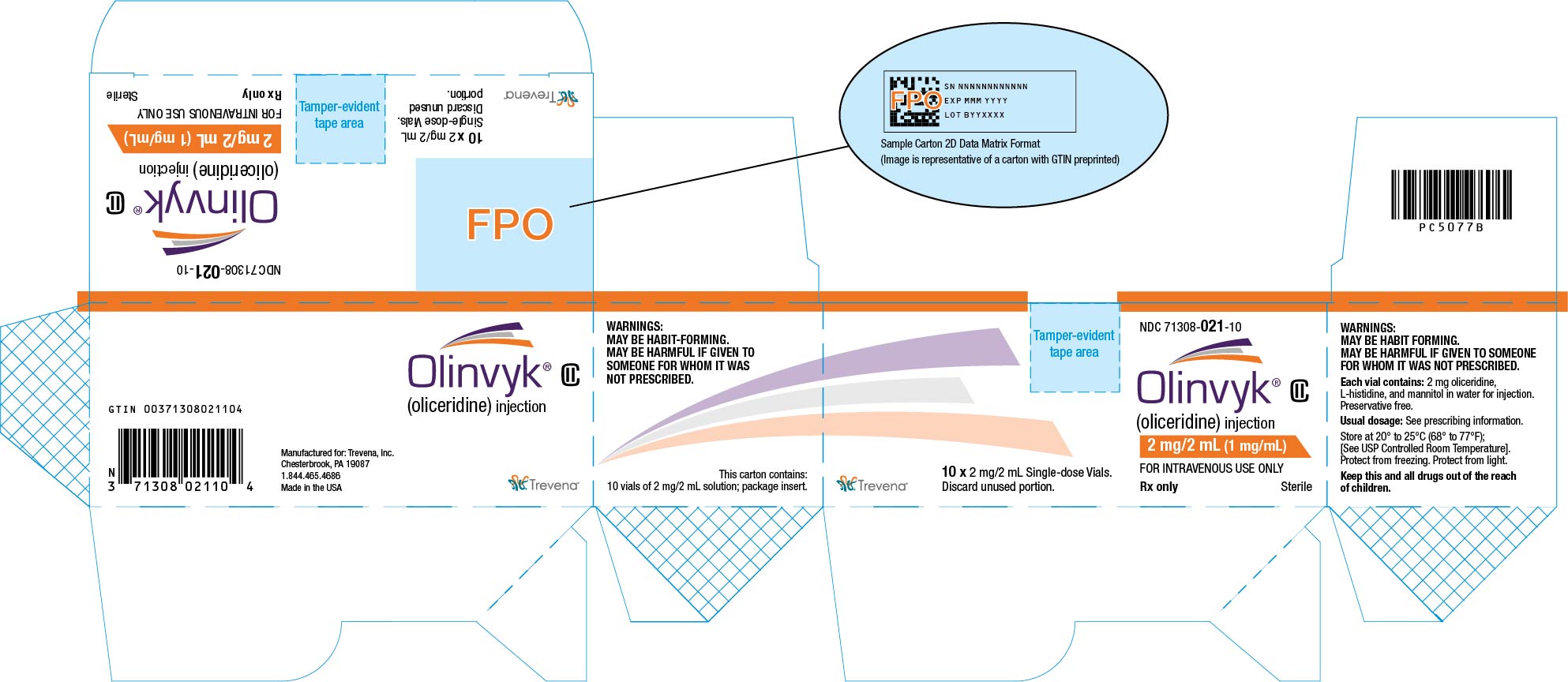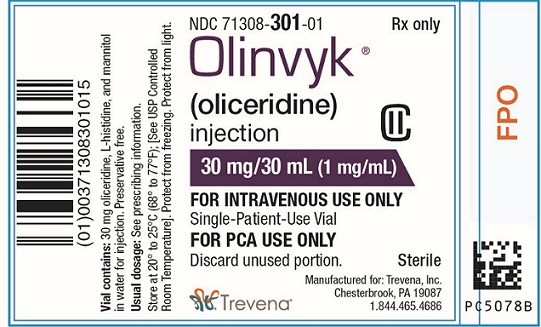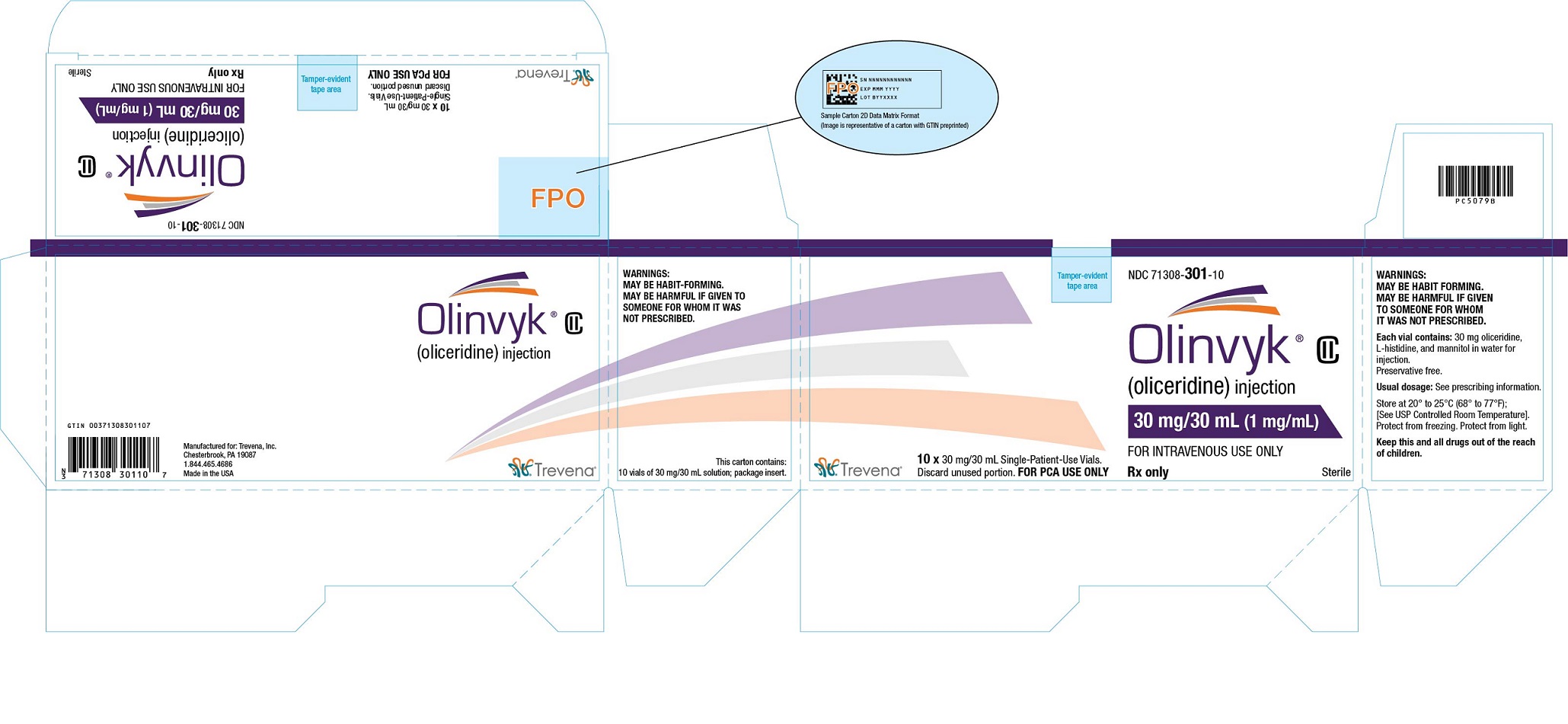 DRUG LABEL: OLINVYK
NDC: 71308-011 | Form: INJECTION, SOLUTION
Manufacturer: Trevena, Inc.
Category: prescription | Type: HUMAN PRESCRIPTION DRUG LABEL
Date: 20251231
DEA Schedule: CII

ACTIVE INGREDIENTS: OLICERIDINE 1 mg/1 mL
INACTIVE INGREDIENTS: HISTIDINE; MANNITOL; WATER

HIGHLIGHTS OF PRESCRIBING INFORMATION

These highlights do not include all the information needed to use OLINVYK® safely and effectively. See full prescribing information for OLINVYK.
OLINVYK (oliceridine) injection, for intravenous use, CII
Initial U.S. Approval: 2020

RECENT MAJOR CHANGES

Boxed Warning 12/2025

Indications and Usage (1) 12/2025

Dosage and Administration (2.4) 12/2025

Warnings and Precautions (5.1, 5.2, 5.3, 5.12, 5.14) 12/2025

WARNING: SERIOUS AND LIFE-THREATENING RISKS FROM USE OF OLINVYK

See full prescribing information for complete boxed warning.

- OLINVYK exposes users to the risks of opioid addiction, abuse, and misuse, which can lead to overdose and death. Assess each patient’s risk before prescribing, and reassess regularly for the development of behaviors or conditions. (5.1)
- Serious, life-threatening, or fatal respiratory depression may occur with use of OLINVYK, especially during initiation or following a dosage increase. To reduce the risk of respiratory depression, proper dosing and titration of OLINVYK are essential. (5.2)
- Concomitant use of OLINVYK with benzodiazepines or other CNS depressants, including alcohol, may result in profound sedation, respiratory depression, coma, and death. Reserve concomitant prescribing for use in patients for whom alternative treatment options are inadequate. (5.4, 7)
- Advise pregnant women using opioids for an extended period of time of the risks of Neonatal Opioid Withdrawal Syndrome, which may be life-threatening if not recognized and treated. Ensure that management by neonatology experts will be available at delivery. (5.3)

1 INDICATIONS AND USAGE

OLINVYK is an opioid agonist indicated in adults for the management of acute pain severe enough to require an intravenous opioid analgesic and for whom alternative treatments are inadequate. (1)

Limitations of Use (1)

Because of the risks of addiction, abuse, misuse, overdose, and death, which can occur at any dosage or duration and persist over the course of therapy, reserve opioid analgesics, including OLINVYK, for use in patients for whom alternative treatment options are ineffective, not tolerated, or would be otherwise inadequate to provide sufficient management of pain.(1, 5.1)

The cumulative total daily dose should not exceed 27 mg. (2.1, 2.2, 5.5).

2 DOSAGE AND ADMINISTRATION

- For intravenous administration only. OLINVYK should be prescribed only by healthcare professionals who are knowledgeable about the use of opioids and how to mitigate the associated risks. (2.1)
- Use the lowest effective dosage for the shortest duration consistent with individual patient treatment goals. Reserve titration to higher doses of OLINVYK for patients in whom lower doses are insufficiently effective and in whom the expected benefits of using a higher dose opioid clearly outweigh the substantial risks. (2.1, 5)
- Initiate the dosing regimen for each patient individually, taking into account the patient’s underlying cause and severity of pain, prior analgesic treatment and response, and risk factors for addiction, abuse and misuse. (2.1, 5.1)
- Respiratory depression can occur at any time during opioid therapy, especially when initiating and following dosage increases with OLINVYK. Consider this risk when selecting an initial dose and when making dose adjustments. (2.1, 5.2)
- Initiate treatment with a 1.5 mg dose. (2.2)
- For patient controlled analgesia (PCA), recommended demand dose is 0.35 mg, with a 6-minute lock-out. A demand dose of 0.5 mg may be considered. (2.2)
- Supplemental doses of 0.75 mg can be administered, beginning 1 hour after the initial dose, and hourly thereafter, as needed. (2.2)
- Periodically reassess patients receiving OLINVYK to evaluate the continued need for opioid analgesics to maintain pain control, for the signs or symptoms of adverse reactions, and for the development of addiction, abuse, or misuse. (2.3)
- Do not rapidly reduce or abruptly discontinue OLINVYK in a physically-dependent patient. (2.4, 5.14)

3 DOSAGE FORMS AND STRENGTHS

Injection:

- 1 mg/mL and 2 mg/2 ml (1 mg/mL) in single-dose vials
- 30 mg/30 mL (1 mg/mL) in single-patient-use vial, For PCA Use Only (3)

4 CONTRAINDICATIONS

- Significant respiratory depression (4)
- Acute or severe bronchial asthma in an unmonitored setting or in absence of resuscitative equipment (4)
- Known or suspected gastrointestinal obstruction, including paralytic ileus (4)
- Known hypersensitivity to oliceridine (4)

5 WARNINGS AND PRECAUTIONS

Opioid-Induced Hyperalgesia and Allodynia: Opioid-Induced Hyperalgesia (OIH) occurs when an opioid analgesic paradoxically causes an increase in pain, or an increase in sensitivity to pain. If OIH is suspected, carefully consider appropriately decreasing the dose of the current opioid analgesic or opioid rotation. (5.7)

Potential for QT Prolongation with Daily Doses Exceeding 27 mg: May increase risk for QT interval prolongation. Do not exceed a cumulative daily dose of 27 mg. (5.5)

Life-Threatening Respiratory Depression in Patients with Chronic Pulmonary Disease or in Elderly, Cachectic, or Debilitated Patients: Monitor closely, particularly during initiation and titration. (5.8)

Adrenal Insufficiency: If diagnosed, treat with physiologic replacement corticosteroids and wean the patient off the opioid. (5.9)

Severe Hypotension: Monitor patients during initiation or titration. Avoid use of OLINVYK in patients with circulatory shock. (5.10)

Risks of Use in Patients with Increased Intracranial Pressure, Brain Tumors, Head Injury, or Impaired Consciousness: Monitor for signs of sedation and respiratory depression. Avoid the use of OLINVYK in patients with impaired consciousness or coma. (5.11)

6 ADVERSE REACTIONS

The most common (incidence ≥10%) adverse reactions in controlled clinical trials (Studies 1 and 2) were nausea, vomiting, dizziness, headache, constipation, pruritus, and hypoxia. (6.1)

To report SUSPECTED ADVERSE REACTIONS, contact Trevena, Inc. at 1-844-465-4686 or FDA at 1-800-FDA-1088 or www.fda.gov/medwatch

7 DRUG INTERACTIONS

Moderate and Strong CYP2D6 and CYP3A4 Inhibitors: Patients may require less frequent dosing. Monitor closely and administer subsequent doses based on severity of pain and patient response. (5.6, 7)

Serotonergic Drugs: Concomitant use may result in serotonin syndrome. Discontinue OLINVYK if serotonin syndrome is suspected. (7)

Mixed Agonist/Antagonist and Partial Agonist Opioid Analgesics: Avoid use with OLINVYK because they may reduce analgesic effect of OLINVYK or precipitate withdrawal symptoms. (7)

8 USE IN SPECIFIC POPULATIONS

Pregnancy: May cause fetal harm (8.1)

Decreased CYP2D6 function: Patients may require less frequent dosing. Monitor closely and administer subsequent doses based on severity of pain and patient response. (8.8)

FULL PRESCRIBING INFORMATION

WARNING: SERIOUS AND LIFE-THREATENING RISKS FROM USE OF OLINVYK

Addiction, Abuse, and Misuse

Because the use of OLINVYK exposes patients and other users to the risks of opioid addiction, abuse, and misuse, which can lead to overdose and death, assess each patient’s risk prior to prescribing and reassess all patients regularly for the development of these behaviors and conditions [see Warnings and Precautions (5.1)].

Life-Threatening Respiratory Depression

Serious, life-threatening, or fatal respiratory depression may occur with use of OLINVYK, especially during initiation or following a dosage increase. To reduce the risk of respiratory depression, proper dosing and titration of OLINVYK are essential [see Warnings and Precautions (5.2)].

Risks From Concomitant Use With Benzodiazepines Or Other CNS Depressants

Concomitant use of opioids with benzodiazepines or other central nervous system (CNS) depressants, including alcohol, may result in profound sedation, respiratory depression, coma, and death. Reserve concomitant prescribing of OLINVYK and benzodiazepines or other CNS depressants for use in patients for whom alternative treatment options are inadequate [see Warnings and Precautions (5.3), Drug Interactions (7)].

Neonatal Opioid Withdrawal Syndrome

Advise pregnant women using opioids for an extended period of time of the risk of Neonatal Opioid Withdrawal Syndrome, which may be life-threatening if not recognized and treated. Ensure that management by neonatology experts will be available at delivery [see Warnings and Precautions (5.4)].

1 INDICATIONS AND USAGE

OLINVYK is indicated in adults for the management of acute pain severe enough to require an intravenous opioid analgesic and for whom alternative treatments are inadequate.

Limitations of Use

Because of the risks of addiction, abuse, misuse, overdose, and death, which can occur at any dosage or duration [see Warnings and Precautions (5.1)], and persist over the course of therapy, reserve opioid analgesics, including OLINVYK, for use in patients for whom alternative treatment options are ineffective, not management of pain.

The cumulative total daily dose should not exceed 27 mg, as total daily doses greater than 27 mg may increase the risk for QTc interval prolongation [see Warnings and Precautions (5.5].

2 DOSAGE AND ADMINISTRATION

2.1 Important Dosage and Administration Instructions

For intravenous administration only.

OLINVYK should be prescribed only by healthcare professionals who are knowledgeable about the use of opioids and how to mitigate the associated risks.

Individual single doses greater than 3 mg have not been evaluated.

The cumulative daily dose should not exceed 27 mg.

OLINVYK 30 mg/30 mL (1mg/mL) vial is intended for patient-controlled analgesia (PCA) use only. Draw OLINVYK directly from the vial into the PCA syringe or IV bag without diluting.

Use the lowest effective dose for the shortest duration consistent with individual patient treatment goals [see Warnings and Precautions (5)]. Because the risk of overdose increases as opioid doses increase, reserve titration to higher doses of OLINVYK for patients in whom lower doses are insufficiently effective and in whom the expected benefits of using a higher dose opioid clearly outweigh the substantial risks.

Use of OLINVYK beyond 48 hours has not been studied in controlled clinical trials.

There is variability in opioid analgesic dose and duration needed to adequately manage pain due both to the cause of pain and to individual patient factors. Initiate the dosing regimen for each patient individually, taking into account the patient's underlying cause and severity of pain, prior analgesic treatment and response, and risk factors for addiction, abuse, and misuse (5.1)].

Respiratory depression can occur at any time during opioid therapy, especially when initiating and following dosage increases with OLINVYK. Consider this risk when selecting an initial dose and when making dose adjustments [see Warnings and Precautions (5)].

Inspect OLINVYK for particulate matter and discoloration prior to administration. The solution is a clear, colorless, preservative free solution for intravenous use. If visibly opaque particles, discoloration, or other foreign particles are observed, do not use.

2.2 Initial Dosage

OLINVYK can be administered by a healthcare provider with an initial dose of 1.5 mg. For PCA, the initial dose can be followed by access to patient demand doses with a 6-minute lock-out. The recommended demand dose is 0.35 mg. A demand dose of 0.5 mg may be considered for some patients if the potential benefit outweighs the risks. Supplemental doses of 0.75 mg OLINVYK can be administered by healthcare providers, beginning 1 hour after the initial dose, and hourly thereafter as needed.

Onset of analgesic effect is expected within 2 to 5 minutes after the initial dose [see Clinical Pharmacology (12.2)].

Do not administer single doses greater than 3 mg [see Adverse Reactions (6.1)].

The cumulative total daily dose should not exceed 27 mg. If patients reach a 27 mg cumulative daily dose and analgesia is still required, an alternative analgesic regimen should be administered until OLINVYK can be resumed the next day. Alternative analgesia may include multi-modal therapies. The safety of OLINVYK beyond 48 hours of use was not evaluated in controlled clinical trials [see Warnings and Precautions (5.5)].

Conversion Between Morphine Intravenous Injection and OLINVYK Intravenous Injection

Based on data collected in clinical studies, an initial 1 mg dose of OLINVYK is approximately equipotent to morphine 5 mg [see Clinical Pharmacology (12.2)]. As individual patients differ in their response to opioid drugs, this comparison should be used only as a guide.

2.3 Titration and Maintenance of Therapy

Titrate the dose based upon the individual patient’s response to their initial dose of OLINVYK. Individually titrate OLINVYK to a dose that provides adequate analgesia and minimizes adverse reactions. Continually reevaluate patients receiving OLINVYK to assess the maintenance of pain control, signs and symptoms of opioid withdrawal, and other adverse reactions, as well as to reassess for the development of addiction, abuse, or misuse [see Warnings and Precautions (5.1, 5.14)]. Frequent communication is important among the prescriber, other members of the healthcare team, the patient, and the caregiver/family during periods of changing analgesic requirements, including initial titration.

If the level of pain increases after dosage stabilization, attempt to identify the source of increased pain before increasing the OLINVYK dosage. If after increasing the dosage, unacceptable opioid-related adverse reactions are observed (including an increase in pain after a dosage increase), consider reducing the dosage [see Warnings and Precautions (5)]. Adjust the dosage to obtain an appropriate balance between management of pain and opioid-related adverse reactions.

2.4 Safe Reduction or Discontinuation of OLINVYK

When a patient who has been taking opioids regularly and may be physically dependent no longer requires therapy with OLINVYK, taper the dose gradually while regularly evaluating for signs and symptoms of withdrawal. If the patient develops these signs or symptoms, raise the dose to the previous level and taper more slowly, either by increasing the interval between decreases, decreasing the amount of change in dose, or both. Do not rapidly reduce or abruptly discontinue OLINVYK in patients who may be physically dependent on opioids [see Warnings and Precautions (5.1, 5.14), Drug Abuse and Dependence (9.3); Nonclinical Toxicology (13.2)].

3 DOSAGE FORMS AND STRENGTHS

Injection: clear, colorless, sterile, preservative-free solution for intravenous use supplied as follows:

- 1 mg/mL, equivalent to 1.3 mg/mL oliceridine fumarate salt, in single-dose, 2 mL, clear glass vials with gray plastic flip-off caps
- 2 mg/2 mL (1 mg/mL), equivalent to 2.6 mg/2 mL (1.3 mg/mL) oliceridine fumarate salt, in single-dose, 2 mL, clear glass vials with orange plastic flip-off caps
- 30 mg/30 mL (1 mg/mL), equivalent to 39 mg/30 mL (1.3 mg/mL) oliceridine fumarate salt, in single-patient-use, 30 mL, clear glass vials with purple plastic flip-off caps. For PCA Use Only.

4 CONTRAINDICATIONS

OLINVYK is contraindicated in patients with:

- Significant respiratory depression [see Warnings and Precautions (5.2)]
- Acute or severe bronchial asthma in an unmonitored setting or in the absence of resuscitative equipment [see Warnings and Precautions (5.8)]
- Known or suspected gastrointestinal obstruction, including paralytic ileus [see Warnings and Precautions (5.12)]
- Known hypersensitivity to oliceridine (e.g., anaphylaxis)

5 WARNINGS AND PRECAUTIONS

5.1 Addiction, Abuse, and Misuse

OLINVYK contains oliceridine, a Schedule II controlled substance. As an opioid, OLINVYK exposes users to the risks of addiction, abuse, and misuse [see Drug Abuse and Dependence (9)].

Although the risk of addiction in any individual is unknown, it can occur in patients appropriately prescribed OLINVYK. Addiction can occur at recommended dosages and if the drug is misused or abused [see Drug Abuse and Dependence (9)]. The risk of opioid-related overdose or overdose-related death is increased with higher opioid doses, and this risk persists over the course of therapy. In postmarketing studies, addiction, abuse, misuse, and fatal and non-fatal opioid overdose were observed in patients with long-term opioid use [see Adverse Reactions (6.2)].

Assess each patient’s risk for opioid addiction, abuse, or misuse prior to prescribing OLINVYK, and monitor all patients receiving OLINVYK for the development of these behaviors or conditions. Risks are increased in patients with a personal or family history of substance abuse (including drug or alcohol abuse or addiction) or mental illness (e.g., major depression). The potential for these risks should not, however, prevent the proper management of pain in any given patient. Patients at increased risk may be prescribed opioids such as OLINVYK, but use in such patients necessitates intensive counseling about the risks and proper use of OLINVYK along with intensive monitoring for signs of addiction, abuse, and misuse.

Opioids are sought for nonmedical use and are subject to diversion from legitimate prescribed use. Consider these risks when prescribing or dispensing OLINVYK. Strategies to reduce these risks include prescribing the drug in the smallest appropriate quantity. Contact local state professional licensing board or state-controlled substances authority for information on how to prevent and detect abuse or diversion of this product.

5.2 Life-Threatening Respiratory Depression

Serious, life-threatening respiratory depression has been reported with the use of opioids, even when used as recommended. Respiratory depression, if not immediately recognized and treated, may lead to respiratory arrest and death. Management of respiratory depression may include close observation, supportive measures, and use of opioid opioid overdose reversal agents (e.g., naloxone, nalmefene), depending on the patient’s clinical status [see Overdosage (10.2)]. Carbon dioxide (CO2) retention from opioid-induced respiratory depression can exacerbate the sedating effects of opioids.

While serious, life-threatening, or fatal respiratory depression can occur at any time during the use of opioids, the risk is greatest during initiation of therapy or following a dose increase. Monitor patients closely for respiratory depression, especially when initiating therapy with OLINVYK and following dosage increases.

To reduce the risk of respiratory depression, proper dosing of OLINVYK is essential [see Dosage and Administration (2)]. Overestimating the OLINVYK dosage when converting patients from another opioid product can result in fatal overdose with the first dose.

Opioids can cause sleep-related breathing disorders including central sleep apnea (CSA) and sleep-related hypoxemia. Opioid use increases the risk of CSA in a dose-dependent fashion. In patients who present with CSA, consider decreasing the opioid dosage using best practices for opioid taper.

5.3 Risks from Concomitant Use with Benzodiazepines or Other CNS Depressants

Profound sedation, respiratory depression, coma, and death may result from the concomitant use of OLINVYK with benzodiazepines and/or other CNS depressants, including alcohol (e.g., non-benzodiazepine sedatives/hypnotics, anxiolytics, tranquilizers, muscle relaxants, general anesthetics, antipsychotics, gabapentinoids [gabapentin or pregabalin], and other opioids, or alcohol). Because of these risks, reserve concomitant prescribing of these drugs for use in patients for whom alternative treatment options are inadequate.

Observational studies have demonstrated that concomitant use of opioid analgesics and benzodiazepines increases the risk of drug-related mortality compared to use of opioid analgesics alone. Because of similar pharmacological properties, it is reasonable to expect similar risk with the concomitant use of other CNS depressant drugs with opioid analgesics [see Drug Interactions (7)].

If the decision is made to prescribe a benzodiazepine or other CNS depressant concomitantly with an opioid analgesic, prescribe the lowest effective dosages and minimum durations of concomitant use. In patients already receiving an opioid analgesic, prescribe a lower initial dose of the benzodiazepine or other CNS depressant than indicated in the absence of an opioid, and titrate based on clinical response. If an opioid analgesic is initiated in a patient already taking a benzodiazepine or other CNS depressant, prescribe a lower initial dose of the opioid analgesic, and titrate based on clinical response. Monitor patients closely for signs and symptoms of respiratory depression and sedation.

5.4 Neonatal Opioid Withdrawal Syndrome

Use of OLINVYK for an extended period of time during pregnancy can result in withdrawal in the neonate. Neonatal opioid withdrawal syndrome, unlike opioid withdrawal syndrome in adults, may be life‑threatening if not recognized and treated, and requires management according to protocols developed by neonatology experts. Observe newborns for signs of neonatal opioid withdrawal syndrome and manage accordingly. Advise women using opioids for an extended period of time of the risk of neonatal opioid withdrawal syndrome and ensure that management by neonatology experts will be available at delivery [see Use in Specific Populations (8.1)].

5.5 Potential for QT prolongation with Daily Doses exceeding 27 mg

The effect of oliceridine on cardiac physiology was studied in single and multiple-dose thorough QT studies. The multiple-dose study was conducted with a maximum daily cumulative dose of 27 mg. In both studies, there was mild QTc interval prolongation. In the multiple-dose study, the maximum mean ΔΔQTcI was 11.7 ms (two-sided 90% UCI 14.7 ms) at 9 hours. The effect on QT prolongation at total cumulative daily doses >27 mg has not been studied in a thorough QT study [see Clinical Pharmacology (12.2)]. Total cumulative daily doses exceeding 27 mg per day may increase the risk for QTc interval prolongation. Therefore, the cumulative total daily dose of OLINVYK should not exceed 27 mg [see Dosage and Administration (2.2)].

5.6 Risk of Use in Patients with Decreased Cytochrome P450 2D6 Function or Concomitant Use or Discontinuation with Cytochrome P450 3A4 Inhibitors and Inducers

Risk of Increased Oliceridine Plasma Concentrations

Increased plasma concentrations of oliceridine, which may result in prolonged opioid adverse reactions and exacerbated respiratory depression, may occur when OLINVYK is used under the following conditions:

- In patients with decreased Cytochrome P450 (CYP) 2D6 function (poor metabolizers of CYP2D6 or normal metabolizers taking moderate or strong CYP2D6 inhibitors) [See Drug Interactions (7); Use in Specific Populations (8.8)].
- In patients taking a moderate or strong CYP3A4 inhibitor
- In patients with decreased CYP2D6 function who are also receiving a moderate or strong CYP3A4 inhibitor
- Discontinuation of a CYP3A4 inducer

These patients may require less frequent dosing of OLINVYK. Closely monitor these patients for respiratory depression and sedation at frequent intervals and base subsequent doses of OLINVYK on the patient’s severity of pain and response to treatment. [see Drug Interactions (7), Use in Specific Populations (8.8), Clinical Pharmacology (12.3, 12.5)].

Risk of Lower than Expected Oliceridine Plasma Concentrations

Lower than expected concentrations of oliceridine, which may lead to decreased efficacy, may occur under the following conditions:

- Concomitant use of OLINVYK with CYP3A4 inducers
- Discontinuation of a moderate or strong CYP3A4 or CYP2D6 inhibitor

Closely monitor these patients at frequent intervals and consider supplemental doses of OLINVYK [see Dosage and Administration (2.2), Drug Interactions (7)].

5.7 Opioid-Induced Hyperalgesia and Allodynia

Opioid-Induced Hyperalgesia (OIH) occurs when an opioid analgesic paradoxically causes an increase in pain, or an increase in sensitivity to pain. This condition differs from tolerance, which is the need for increasing doses of opioids to maintain a defined effect [see Dependence (9.3)]. Symptoms of OIH include (but may not be limited to) increased levels of pain upon opioid dosage increase, decreased levels of pain upon opioid dosage decrease, or pain from ordinarily non-painful stimuli (allodynia). These symptoms may suggest OIH only if there is no evidence of underlying disease progression, opioid tolerance, opioid withdrawal, or addictive behavior.

Cases of OIH have been reported, both with short-term and longer-term use of opioid analgesics. Though the mechanism of OIH is not fully understood, multiple biochemical pathways have been implicated. Medical literature suggests a strong biologic plausibility between opioid analgesics and OIH and allodynia. If a patient is suspected to be experiencing OIH, carefully consider appropriately decreasing the dose of the current opioid analgesic or opioid rotation (safely switching the patient to a different opioid moiety) [see Dosage and Administration (2.4); Warnings and Precautions (5.7)].

5.8 Life-Threatening Respiratory Depression in Patients with Chronic Pulmonary Disease or in Elderly, Cachectic, or Debilitated Patients

The use of OLINVYK in patients with acute or severe bronchial asthma in an unmonitored setting or in the absence of resuscitative equipment is contraindicated.

Patients with Chronic Pulmonary Disease: OLINVYK-treated patients with significant chronic obstructive pulmonary disease or cor pulmonale, and those with a substantially decreased respiratory reserve, hypoxia, hypercapnia, or preexisting respiratory depression are at increased risk of decreased respiratory drive including apnea, even at recommended dosages of OLINVYK [see Warnings and Precautions (5.2)].

Elderly, Cachectic, or Debilitated Patients: Life-threatening respiratory depression is more likely to occur in elderly, cachectic, or debilitated patients as they may have altered pharmacokinetics or altered clearance compared to younger, healthier patients [see Warnings and Precautions (5.2)].

Monitor such patients closely, particularly when initiating and titrating OLINVYK and when OLINVYK is given concomitantly with other drugs that depress respiration [see Warnings and Precautions (5.2, 5.3); Drug Interactions (7)]. Alternatively, consider the use of non-opioid analgesics in these patients.

5.9 Adrenal Insufficiency

Cases of adrenal insufficiency have been reported with opioid use, more often following greater than one month of use. Presentation of adrenal insufficiency may include non-specific symptoms and signs including nausea, vomiting, anorexia, fatigue, weakness, dizziness, and low blood pressure. If adrenal insufficiency is suspected, confirm the diagnosis with diagnostic testing as soon as possible. If adrenal insufficiency is diagnosed, treat with physiologic replacement doses of corticosteroids. Wean the patient off of the opioid to allow adrenal function to recover and continue corticosteroid treatment until adrenal function recovers. Other opioids may be tried as some cases reported use of a different opioid without recurrence of adrenal insufficiency. The information available does not identify any particular opioids as being more likely to be associated with adrenal insufficiency.

5.10 Severe Hypotension

OLINVYK may cause severe hypotension, including orthostatic hypotension and syncope in ambulatory patients. There is increased risk in patients whose ability to maintain blood pressure has already been compromised by a reduced blood volume or concurrent administration of certain CNS depressant drugs (e.g., phenothiazines or general anesthetics) [see Drug Interactions (7)]. Monitor these patients for signs of hypotension after initiating or titrating the dosage of OLINVYK. In patients with circulatory shock, OLINVYK may cause vasodilation that can further reduce cardiac output and blood pressure. Avoid the use of OLINVYK in patients with circulatory shock.

5.11 Risks of Use in Patients with Increased Intracranial Pressure, Brain Tumors, Head Injury, or Impaired Consciousness

In patients who may be susceptible to the intracranial effects of CO2 retention (e.g., those with evidence of increased intracranial pressure or brain tumors), OLINVYK may reduce respiratory drive, and the resultant CO2 retention can further increase intracranial pressure. Monitor such patients for signs of sedation and respiratory depression, particularly when initiating therapy with OLINVYK.

Opioids may also obscure the clinical course in a patient with a head injury. Avoid the use of OLINVYK in patients with impaired consciousness or coma.

5.12 Risks of Gastrointestinal Complications

OLINVYK is contraindicated in patients with known or suspected gastrointestinal obstruction, including paralytic ileus.

The oliceridine in OLINVYK may cause spasm of the sphincter of Oddi. Opioids may cause increases in serum amylase. Monitor patients with biliary tract disease, including acute pancreatitis, for worsening symptoms.

Cases of opioid-induced esophageal dysfunction (OIED) have been reported in patients taking opioids. The risk of OIED may increase as the dose and/or duration of opioids increases. Regularly evaluate patients for signs and symptoms of OIED (e.g., dysphagia, regurgitation, non-cardiac chest pain) and, if necessary, adjust opioid therapy as clinically appropriate [see Clinical Pharmacology (12.2)].

5.13 Increased Risk of Seizures in Patients with Seizure Disorders

OLINVYK may increase the frequency of seizures in patients with seizure disorders, and may increase the risk of seizures occurring in other clinical settings associated with seizures. Monitor patients with a history of seizure disorders for worsened seizure control during OLINVYK therapy.

5.14 Withdrawal

Do not rapidly reduce or abruptly discontinue OLINVYK in a patient physically dependent on opioids. When discontinuing OLINVYK in a physically-dependent patient, gradually taper the dosage. Rapid tapering of oliceridine in a patient physically dependent on opioids may lead to a withdrawal syndrome and return of pain [see Dosage and Administration (2.4), Drug Abuse and Dependence (9.3), Nonclinical Toxicology (13.2)].

Additionally, avoid the use of mixed agonist/antagonist (e.g, pentazocine, nalbuphine, and butorphanol) or partial agonist (e.g., buprenorphine) analgesics in patients who are receiving a full opioid agonist analgesic, including OLINVYK. In these patients, mixed agonist/antagonist and partial agonist analgesics may reduce the analgesic effect and/or precipitate withdrawal symptoms [see Drug Interactions (7)].

5.15 Risks of Driving and Operating Machinery

OLINVYK may impair the mental or physical abilities needed to perform potentially hazardous activities such as driving a car or operating machinery. Warn patients not to drive or operate dangerous machinery unless they are tolerant to the effects of OLINVYK and know how they will react to the medication.

5.16 Patient-Controlled Analgesia (PCA)

Although self-administration of opioids by PCA may allow each patient to individually titrate to an acceptable level of analgesia, PCA administration has resulted in adverse outcomes and episodes of respiratory depression. Health care providers and family members monitoring patients receiving PCA analgesia should be instructed in the need for appropriate monitoring for excessive sedation, respiratory depression, or other adverse effects of opioid medications.

6 ADVERSE REACTIONS

The following adverse reactions are described, or described in greater detail, in other sections:

- Addiction, Abuse, and Misuse [see Warnings and Precautions (5.1)]
- Life-threatening Respiratory Depression [see Warnings and Precautions (5.2)]
- Interactions with Benzodiazepines or Other CNS Depressants [see Warnings and Precautions (5.3)]
- Neonatal Opioid Withdrawal Syndrome [see Warnings and Precautions (5.4)]
- Opioid-Induced Hyperalgesia and Allodynia [see Warnings and Precautions (5.7)]
- Adrenal Insufficiency [see Warnings and Precautions (5.9)]
- Severe Hypotension [see Warnings and Precautions (5.10)]
- Gastrointestinal Adverse Reactions [see Warnings and Precautions (5.12)]
- Seizures [see Warnings and Precautions (5.13)]
- Withdrawal [see Warnings and Precautions (5.14)]

6.1 Clinical Studies Experience

Because clinical trials are conducted under widely varying conditions, adverse reaction rates observed in the clinical trials of a drug cannot be directly compared to rates in the clinical trials of another drug and may not reflect the rates observed in clinical practice.

A total of 1535 patients were treated with OLINVYK in controlled and open-label trials in patients with moderate to severe acute pain. Of these, 1181 patients received a total daily dose ≤27 mg and 354 patients received a total daily dose >27 mg during the first 24-hour treatment period. Among patients who received a daily dose of >27 mg, 198 patients received a daily dose between 27 mg and 40 mg, and 142 patients received a daily dose >40 mg.

The most common adverse drug reactions (≥10%) in controlled efficacy trials (Study 1 and Study 2) were nausea, vomiting, dizziness, headache, constipation, pruritus and hypoxia. Adverse reactions leading to discontinuation of OLINVYK were hypotension, hypoxia, nausea, hypoventilation, oxygen saturation decreased, alanine aminotransferase increased, aspartate aminotransferase increased, electrocardiogram QT prolongation, and urticaria. In two randomized, double-blind, placebo- and morphine-controlled studies, when stratified by 27 mg daily dosing limit, discontinuation of OLINVYK due to adverse reactions occurred in 4% of patients who received a daily dose ≤ 27 mg, and less than 1% of patients who received a daily dose >27 mg. In these same studies, discontinuation due to adverse reactions occurred in 5% of morphine-treated patients, and no placebo-treated patients. In an open-label safety study, discontinuation of OLINVYK due to adverse drug reactions occurred in 3% of patients who received a daily dose ≤ 27 mg, and 1% of patients who received a daily dose >27 mg.

In two randomized, double-blind, placebo- and morphine-controlled studies in patients with moderate to severe acute pain following either orthopedic surgery-bunionectomy (Study 1), or plastic surgery-abdominoplasty (Study 2), patients received one of three OLINVYK dosing regimens, a morphine- control regimen, or a volume‑matched placebo-control regimen. All dosing regimens were administered via patient-controlled analgesia (PCA), allowing patients to individually titrate the dose available to an acceptable level of analgesia. Patients were treated for up to 48 hours in the bunionectomy study (Study 1), and for up to 24 hours in the abdominoplasty study(Study 2) [see Clinical Studies (14)]. The loading dose for all OLINVYK treatment regimens was 1.5 mg; demand doses were 0.1, 0.35, or 0.5 mg, according to assigned treatment group; supplemental doses of 0.75 mg were permitted, beginning 1 hour after the loading dose, and hourly thereafter, as needed. The loading dose for the morphine treatment regimen was 4 mg; the demand dose was 1 mg; and supplemental doses of 2 mg were permitted, beginning 1 hour after the loading dose, and hourly thereafter, as needed. A lockout interval of 6 minutes was used for all PCA regimens.

In Study 1, a total of 136 patients received OLINVYK ≤27 mg/day, and 98 patients received OLINVYK >27 mg/day during the first 24 hours. In Study 2, a total of 180 patients received OLINVYK ≤27 mg/day, and 56 patients received OLINVYK >27 mg/day during the first 24 hours.

Table 1 and Table 2 list adverse drug reactions that were reported in ≥5% of OLINVYK-treated patients in each study, and that occurred at a frequency greater than placebo in at least one of the studies. Table 2 and Table 3 lists adverse drug reactions that were reported in ≥5% of OLINVYK-treated patients for pooled Studies 1 and 2 stratified by total daily dose (≤27 mg/day or >27 mg/day).

These data are not an adequate basis for comparison of rates between the OLINVYK treatment group and the morphine treatment group. The OLINVYK and morphine dosing regimens studied are not considered equipotent.

Table 1: Adverse Drug Reactions Reported in ≥5% of OLINVYK-Treated Patients Following Orthopedic Surgery-Bunionectomy (Study 1)
Adverse Drug Reaction | Placebo (N = 79) | OLINVYK 0.35 mga (N = 79) | OLINVYK 0.5 mga (N = 79) | Morphineb (N = 76)
Patients with any TEAEc (%) | 68 | 86 | 91 | 96
Nausea | 24 | 56 | 63 | 65
Vomiting | 6 | 39 | 41 | 50
Dizziness | 10 | 32 | 35 | 34
Somnolence | 6 | 19 | 13 | 13
Constipation | 11 | 11 | 14 | 17
Pruritus | 8 | 15 | 4 | 20
Hypoxia | 0 | 5 | 9 | 9
Sedation | 1 | 5 | 4 | 3
Oxygen saturation decreased | 0 | 4 | 5 | 9
a Each OLINVYK regimen included a loading dose of 1.5 mg, followed by access to demand doses of 0.35 or 0.5 mg, with a 6-minute lockout period between doses, and 0.75-mg supplemental doses, beginning 1 hour after the initial dose, and hourly thereafter, as needed.
b The morphine regimen included a loading dose of 4 mg, followed by access to a demand dose of 1 mg, with a 6-minute lockout period between doses, and 2-mg supplemental doses, beginning 1 hour after the initial dose, and hourly thereafter, as needed.
c Treatment Emergent Adverse Event

Table 2: Adverse Drug Reactions Reported in ≥5% of OLINVYK -Treated Patients Following Plastic Surgery-Abdominoplasty (Study 2)
Adverse Drug Reaction | Placebo (N = 83) | OLINVYK 0.35 mga (N = 79) | OLINVYK 0.5 mga (N = 80) | Morphineb (N = 82)
Patients with any TEAEc (%) | 78 | 94 | 95 | 98
Nausea | 46 | 62 | 75 | 74
Vomiting | 13 | 22 | 43 | 54
Hypoxia | 5 | 20 | 18 | 23
Constipation | 7 | 17 | 11 | 11
Pruritus | 5 | 17 | 11 | 18
Dizziness | 11 | 9 | 9 | 16
Sedation | 8 | 14 | 9 | 23
Back pain | 6 | 13 | 11 | 9
Somnolence | 1 | 0 | 5 | 7
a Each OLINVYK regimen included a loading dose of 1.5 mg, followed by access to demand doses of 0.35 or 0.5 mg with a 6-minute lockout period between doses, and 0.75-mg supplemental doses beginning 1 hour after the initial dose and hourly thereafter as needed.
b The morphine regimen included a loading dose of 4 mg, followed by access to a demand dose of 1 mg with a 6-minute lockout period between doses, and 2-mg supplemental doses beginning 1 hour after the initial dose, and hourly thereafter, as needed.
c Treatment Emergent Adverse Event

Table 3: Adverse Drug Reactions Reported in ≥5% of OLINVYK-Treated Patients Stratified by Daily Dose (Study 1 and 2 Pooled)
Adverse Drug Reaction | Placebo; (N = 162) | OLINVYK ≤ 27 mg (N = 316) | OLINVYK > 27 mg (N= 154) | Morphine; (N =158)
Patients with any TEAEa (%) | 73 | 86 | 92 | 96
Nausea | 35 | 52 | 66 | 70
Vomiting | 10 | 26 | 42 | 52
Headache | 30 | 26 | 26 | 30
Dizziness | 11 | 18 | 27 | 25
Constipation | 9 | 14 | 12 | 14
Hypoxia | 3 | 12 | 6 | 17
Pruritus | 6 | 9 | 14 | 19
Sedation | 5 | 7 | 7 | 13
Somnolence | 4 | 6 | 10 | 10
Back pain | 4 | 6 | 4 | 6
Hot flush | 4 | 4 | 7 | 8
Pruritus generalized | 1 | 2 | 5 | 10
a Treatment Emergent Adverse Event

In an open-label safety study of patients with moderate to severe acute pain following a surgical procedure or due to a medical condition (Study 3), a total of 768 patients received at least one dose of OLINVYK. OLINVYK was administered via clinician-administered bolus dosing, PCA, or a combination of the two. Bolus dosing was initiated at 1 to 2 mg, with supplemental doses of 1 to 3 mg every 1 to 3 hours, as needed, based on individual patient need and previous response to OLINVYK. If OLINVYK was administered via PCA, the loading dose was 1.5 mg, the demand dose was 0.5 mg, and the lockout interval was 6 minutes. Supplemental doses of 1 mg were given as needed, taking into account the patient's utilization of PCA demand doses, individual patient need, and previous response to OLINVYK.

In Study 3, for the patients within the highest cumulative dose group (exposure >36 mg), the mean cumulative exposure was 67 mg (range: 37 mg to 224 mg) and the mean cumulative duration of exposure was 54 hours (range: 6 hours to 143 hours). The mean cumulative dose of OLINVYK administered to patients in the Study 3 was 30 mg over a mean cumulative duration of 29 hours. The most frequent condition treated in Study 3 was post-surgical acute pain, and included (in order of decreasing frequency): orthopedic, gynecologic, colorectal, general, plastic, urologic, neurologic (including spinal), bariatric, and cardiothoracic surgical procedures. In Study 3, of the 768 patients treated with OLINVYK, 32% were age 65 years or older and 78% had a Body Mass Index ≥25 kg/m^2. OLINVYK was administered as needed; 55% of patients received OLINVYK via clinician bolus administration only, and 45% of patients received OLINVYK via PCA self-administration or a combination of clinician bolus- and PCA self-administration.

In Study 3 (open-label), a total of 592 patients received OLINVYK ≤27 mg/day and 176 received OLINVYK >27 mg during the first 24 hours. Adverse drug reactions reported in ≥5% of patients receiving OLINVYK in Study 3, stratified by total daily dose (≤27 mg/day or >27 mg/day), are presented in Table 4.

Table 4: Adverse Drug Reactions Reported in ≥5% OLINVYK-Treated Patients in Study 3 (Open-Label)
Adverse Drug Reaction | OLINVYK ≤ 27mg N = 592 | OLINVYK > 27mg N = 176
Patients with any TEAEa (%) | 62 | 69
Nausea | 29 | 38
Constipation | 10 | 13
Vomiting | 9 | 15
Headache | 4 | 5
Hypokalaemia | 4 | 7
Pruritus | 4 | 8
Pyrexia | 3 | 5
a Treatment Emergent Adverse Event

Adverse Drug Reactions Reported in >1% to <5% of Patients in the controlled and open-label studies (Study 1, Study 2, and Study 3) are listed in descending order of frequency within System Organ Class in Table 5.

Table 5: Adverse Drug Reactions Reported in >1% to <5% of Patients in Studies 1-3
System Organ Class | Adverse Drug Reaction Preferred Term
Blood and lymphatic disorders | Anemia
Cardiac disorders | Tachycardia
Gastrointestinal disorders | Flatulence, Dry mouth, Dyspepsia, Diarrhea
General disorders and administration site conditions | Pyrexia, Infusion site extravasation
Injury, poisoning and procedural complications | Procedural nausea
Investigations | Oxygen saturation decreased, Alanine aminotransferase increased, Blood pressure increased
Metabolism and nutritional disorders | Hypokalaemia, Hypocalcaemia, Hypophosphataemia, Hypomagnesaemia
Musculoskeletal and connective tissue disorders | Muscle spasms
Nervous system disorders | Headache
Psychiatric disorders | Anxiety, Insomnia, Restlessness
Respiratory, thoracic and mediastinal disorders | Cough, Dyspnea
Skin and subcutaneous tissue disorders | Hyperhidrosis, Rash, Pruritus generalised
Vascular disorders | Hypotension, Hot flush, Flushing

6.2 Postmarketing Experience

Serotonin syndrome: Cases of serotonin syndrome, a potentially life-threatening condition, have been reported during concomitant use of opioids with serotonergic drugs.

Adrenal insufficiency: Cases of adrenal insufficiency have been reported with opioid use, more often following greater than one month of use.

Anaphylaxis: Anaphylaxis has been reported with ingredients contained in OLINVYK.

Androgen deficiency: Cases of androgen deficiency have occurred with use of opioids for an extended period of time [see Clinical Pharmacology (12.2)].

Hyperalgesia and Allodynia: Cases of hyperalgesia and allodynia have been reported with opioid therapy of any duration [see Warnings and Precautions (5.7)].

Hypoglycemia: Cases of hypoglycemia have been reported in patients taking opioids. Most reports were in patients with at least one predisposing risk factor (e.g., diabetes).

Opioid-induced esophageal dysfunction (OIED): Cases of OIED have been reported in patients taking opioids and may occur more frequently in patients taking higher doses of opioid, and/or in patients taking opioids longer term [see Warnings and Precautions (5.12)].

Adverse Reactions from Observational Studies

A prospective, observational cohort study estimated the risks of addiction, abuse, and misuse in patients initiating long-term use of Schedule II opioid analgesics between 2017 and 2021. Study participants include in one or more analyses had been enrolled in selected insurance plans or health systems for at least one year, were free of at least one outcome at baseline, completed a minimum number of follow-up assessments, and either: 1) filled multiple extended-release/long-acting opioid analgesic prescriptions during a 90-day period (n=978); or 2) filled any Schedule II opioid analgesic prescriptions covering at least 70 of 90 days (n=1,244). Those included also had no dispensing of the qualifying opioids in the previous 6 months.

Over 12 months:

- approximately 1% to 6% of participants across the two cohorts newly met criteria for addiction, as assessed with two validated interview-based measures of moderate-to-severe opioid use disorder based on Diagnostic and Statistical Manual of Mental Disorders, Fifth Edition (DSM-5) criteria, and
- approximately 9% and 22% of participants across the two cohorts newly met criteria for prescription opioid abuse and misuse [defined in Drug Abuse and Dependence (9.2)], respectively, as measured with a validated self-reported instrument.

A retrospective, observational cohort study estimated the risk of opioid-involved overdose or opioid overdose-related death in patients with new long-term use of Schedule II opioid analgesics from 2006 through 2016 (n=220,249). Included patients had been enrolled in either one of two commercial insurance programs, one managed care program, or one Medicaid program for at least 9 months. New long-term use was defined as having Schedule II opioid analgesic prescriptions covering at least 70 days’ supply over the 3 months prior to study entry and none during the preceding 6 months. Patients were excluded if they had an opioid-involved overdose in the 9 months prior to study entry. Overdose was measured using a validated medical code-based algorithm with linkage to the National Death Index database. The 5-year cumulative incidence estimates for opioid-involved overdose or opioid overdose-related death ranged from approximately 1.5% to 4% across study sites, counting only the first event during follow-up. Approximately 17% of first opioid overdoses observed over the entire study period (5-11 years, depending on the study site) were fatal. Higher baseline opioid dose was the strongest and most consistent predictor of opioid-involved overdose or opioid overdose-related death. Study exclusion criteria may have selected patients at lower risk of overdose, and substantial loss to follow-up (approximately 80%) also may have biased estimates.

The risk estimates from the studies described above may not be generalizable to all patients receiving opioid analgesics, such as those with exposures shorter or longer than the duration evaluated in the studies.

7 DRUG INTERACTIONS

Table 6 includes clinically significant drug interactions with OLINVYK.

Table 6: Clinically Significant Drug Interactions with OLINVYK
Moderate to Strong Inhibitors of CYP2D6
Clinical Impact: | Concomitant administration of a moderate to strong CYP2D6 inhibitor can increase the plasma concentration of oliceridine [see Clinical Pharmacology (12.3)], resulting in increased or prolonged opioid effects.
Intervention: | If concomitant use is necessary, patients taking a moderate to strong CYP2D6 inhibitor may require less frequent dosing of OLINVYK. Monitor closely for respiratory depression and sedation at frequent intervals and base subsequent doses on the patient’s severity of pain and response to treatment. If a CYP2D6 inhibitor is discontinued, increase of the OLINVYK dosage may be considered until stable drug effects are achieved. Monitor for signs of opioid withdrawal.
Examples: | Paroxetine, fluoxetine, quinidine, bupropion
Moderate to Strong Inhibitors of CYP3A4
Clinical Impact: | The concomitant administration of moderate to strong CYP3A4 inhibitors can increase the plasma concentration of oliceridine, resulting in increased or prolonged opioid adverse reactions. After stopping a CYP3A4 inhibitor, as the effects of the inhibitor decline, the oliceridine concentration may decrease, resulting in decreased opioid efficacy or a withdrawal syndrome in patients who had developed physical dependence to oliceridine [see Warnings and Precautions (5.14)].
Intervention: | Caution should be used when administering OLINVYK to patients taking inhibitors of the CYP3A4 enzyme. If concomitant use is necessary, patients taking a CYP3A4 inhibitor may require less frequent dosing. Monitor patients for respiratory depression and sedation at frequent intervals. If a CYP3A4 inhibitor is discontinued, increase of the OLINVYK dosage may be considered until stable drug effects are achieved. Monitor for signs of opioid withdrawal.
Examples: | Macrolide antibiotics (e.g., erythromycin), azole-antifungal agents (e.g. ketoconazole), protease inhibitors (e.g., ritonavir).
Strong and Moderate CYP3A4 Inhibitors and CYP2D6 Inhibitors
Clinical Impact: | OLINVYK is primarily metabolized by both CYP3A4 and CYP2D6. Compared to inhibition of either metabolic pathway, inhibition of both pathways can result in a greater increase of the plasma concentrations of oliceridine and prolong opioid adverse reactions [See Clinical Pharmacology (12.3)].
Intervention: | Patients who are CYP2D6 normal metabolizers taking a CYP2D6 inhibitor, and a strong CYP3A4 inhibitor (or discontinuation of CYP3A4 inducers) may require less frequent dosing.; Patients who are known CYP2D6 poor metabolizers and taking a CYP3A4 inhibitor (or discontinuation of CYP3A4 inducers) may require less frequent dosing.; These patients should be closely monitored for respiratory depression and sedation at frequent intervals, and subsequent doses should be based on the patient’s severity of pain and response to treatment.
Examples: | Inhibitors of CYP3A4: Macrolide antibiotics (e.g., erythromycin), azole-antifungal agents (e.g., ketoconazole, itraconazole), anti-retroviral agents, selective serotonin re-uptake inhibitors (SSRIs), protease inhibitors (e.g., ritonavir), NS3/4A inhibitors.; Inhibitors of CYP2D6: Paroxetine, fluoxetine, quinidine, bupropion
Inducers of CYP3A4
Clinical Impact: | The concomitant use of OLINVYK and CYP3A4 inducers can decrease the plasma concentration of oliceridine [see Clinical Pharmacology (12.3)], resulting in decreased efficacy or onset of a withdrawal syndrome in patients who have developed physical dependence to oliceridine. [see Warnings and Precautions (5.14)]. After stopping a CYP3A4 inducer, as the effects of the inducer decline, the oliceridine plasma concentration may increase [see Clinical Pharmacology (12.3)], which could increase or prolong both the therapeutic effects and adverse reactions, and may cause serious respiratory depression.
Intervention: | If concomitant use with CYP3A4 inducer is necessary, increase of the OLINVYK dosage may be considered until stable drug effects are achieved. Monitor for signs of opioid withdrawal. If a CYP3A4 inducer is discontinued, consider OLINVYK dosage reduction and monitor for signs of respiratory depression.
Examples: | Rifampin, carbamazepine, phenytoin
Benzodiazepines and Other Central Nervous System (CNS) Depressants
Clinical Impact: | Due to additive pharmacologic effect, the concomitant use of benzodiazepines or other CNS depressants, including alcohol, increases the risk of hypotension, respiratory depression, profound sedation, coma, and death [see Warnings and Precautions (5.3)].
Intervention: | Reserve concomitant prescribing of these drugs for use in patients for whom alternative treatment options are inadequate. Limit dosages and durations to the minimum required. Monitor closely for signs of respiratory depression and sedation [see Warnings and Precautions (5.3)].
Examples: | Benzodiazepines and other sedatives/hypnotics, anxiolytics, tranquilizers, muscle relaxants, general anesthetics, antipsychotics, gabapentinoids (gabapentin or pregabalin), other opioids, alcohol
Serotonergic Drugs
Clinical Impact: | The concomitant use of opioids with other drugs that affect the serotonergic neurotransmitter system has resulted in serotonin syndrome.
Intervention: | If concomitant use is warranted, carefully observe the patient, particularly during treatment initiation and dose adjustment. Discontinue OLINVYK if serotonin syndrome is suspected.
Examples: | Selective serotonin reuptake inhibitors (SSRIs,) serotonin and norepinephrine reuptake inhibitors (SNRIs), tricyclic antidepressants (TCAs), triptans, 5-HT3 receptor antagonists, drugs that effect the serotonin neurotransmitter system (e.g., mirtazapine, trazodone, tramadol), certain muscle relaxants (i.e., cyclobenzaprine, metaxalone), monoamine oxidase (MAO) inhibitors (those intended to treat psychiatric disorders and also others, such as linezolid and intravenous methylene blue).
Mixed Agonist/Antagonist and Partial Agonist Opioid Analgesics
Clinical Impact: | May reduce the analgesic effect of OLINVYK and/or precipitate withdrawal symptoms.
Intervention: | Avoid concomitant use.
Examples: | butorphanol, nalbuphine, pentazocine, buprenorphine
Muscle Relaxants
Clinical Impact: | OLINVYK may enhance the neuromuscular blocking action of skeletal muscle relaxants and produce an increased degree of respiratory depression.
Intervention: | Monitor patients for signs of respiratory depression that may be greater than otherwise expected and decrease the dosage of OLINVYK and/or the muscle relaxant as necessary.
Examples: | cyclobenzaprine, metaxalone
Diuretics
Clinical Impact: | Opioids can reduce the efficacy of diuretics by inducing the release of antidiuretic hormone.
Intervention: | Monitor patients for signs of diminished diuresis and/or effects on blood pressure and increase the dosage of the diuretic as needed.
Anticholinergic Drugs
Clinical Impact: | The concomitant use of anticholinergic drugs may increase risk of urinary retention and/or severe constipation, which may lead to paralytic ileus.
Intervention: | Monitor patients for signs of urinary retention or reduced gastric motility when OLINVYK is used concomitantly with anticholinergic drugs.

8 USE IN SPECIFIC POPULATIONS

8.1 Pregnancy

Risk Summary

Use of opioid analgesics for an extended period of time during pregnancy may result in neonatal opioid withdrawal syndrome [see Warnings and Precautions (5.4)]. There are no available data on OLINVYK use in pregnant women to evaluate for a drug-associated risk of major birth defects and miscarriage or adverse maternal outcomes. There are adverse outcomes reported within detal exposure to opioid analgesics (see Clinical Considerations).

In animal reproductive studies, oliceridine reduced live litter size at birth and increased postnatal pup mortality between birth and Postnatal Day 4 when administered intravenously to rats from organogenesis through weaning at doses producing clinically relevant plasma exposure. Oliceridine had no effect on embryo-fetal development in rats and rabbits when administered intravenously during organogenesis at doses producing plasma exposures 7 and 8 times the estimated plasma exposure at the maximum recommended human dose (MRHD) on an AUC basis, respectively (see Data).

The background risk of major birth defects and miscarriage for the indicated population is unknown. All pregnancies have a background risk of birth defect, loss, or other adverse outcomes. In the U.S. general population, the estimated background risk of major birth defects and miscarriage in clinically recognized pregnancies is 2 to 4% and 15 to 20%, respectively.

Clinical Considerations

Fetal/Neonatal Adverse Reactions

Use of opioid analgesics for an extended period of time during pregnancy for medical or nonmedical purposes can result in physical dependence in the neonate and neonatal opioid withdrawal syndrome shortly after birth.

Neonatal opioid withdrawal syndrome presents as irritability, hyperactivity and abnormal sleep pattern, high-pitched cry, tremor, vomiting, diarrhea, and failure to gain weight. The onset, duration, and severity of neonatal opioid withdrawal syndrome vary based on the specific opioid used, duration of use, timing and amount of last maternal use, and rate of elimination of the drug by the newborn. Observe newborns for symptoms of neonatal opioid withdrawal syndrome and manage accordingly [see Warnings and Precautions (5.4)].

Labor or Delivery

Opioids cross the placenta and may produce respiratory depression and psycho-physiologic effects in neonates. An opioid overdose reversal agent, such as naloxone or nalmefene, should be available for reversal of opioid induced respiratory depression in the neonate. OLINVYK is not recommended for use in pregnant women during and immediately prior to labor, when other analgesic techniques are more appropriate. Opioid analgesics can prolong labor through actions that temporarily reduce the strength, duration, and frequency of uterine contractions. However, this effect is not consistent and may be offset by an increased rate of cervical dilatation, which tends to shorten labor. Monitor neonates exposed to OLINVYK during labor for signs of excess sedation and respiratory depression.

Data

Animal Data

Oliceridine administered via continuous intravenous infusion during the period of embryofetal organogenesis at doses of 6, 12, or 24 mg/kg/day to pregnant rats from Gestation Day (GD) 6 to 20 and 1.5, 3, or 6 mg/kg/day to pregnant rabbits from GD 7 to 29 had no effect on embryonic development at exposures 7 (rats) to 8 times (rabbits) the estimated plasma exposure at the MRHD of 27 mg/day on an AUC basis. Maternal toxicity (reduced body weight gain) was observed at ≥12 mg/kg/day in rats and at 6 mg/kg/day in rabbits.

In a pre−and post−natal development study in rats, oliceridine administered via continuous intravenous infusion at doses of 0.6, 2.4, and 6.0 mg/kg/day from Gestation Day 6 through Lactation Day 21 resulted in reduced live litter size at birth at 1.5 times the estimated plasma exposure at the MRHD on an AUC basis and lower pup survival between birth and Postnatal Day 4 at 0.6 times the estimated plasma exposure at the MRHD on an AUC basis.

8.2 Lactation

Risk Summary

It is not known whether oliceridine is present in human milk. The effects of oliceridine on a breastfeeding infant and on milk production have not been evaluated.

The developmental and health benefits of breastfeeding should be considered along with the mother’s clinical need for OLINVYK and any potential adverse effects on the breastfed infant from OLINVYK or from the underlying maternal condition.

Clinical Considerations

Monitor infants exposed to OLINVYK through breast milk for excess sedation and respiratory depression. Withdrawal symptoms can occur in breastfed infants when maternal administration of an opioid analgesic is stopped or when breastfeeding is stopped.

8.3 Females and Males of Reproductive Potential

Infertility

Human Data

Use of opioids for an extended period of time may cause reduced fertility in females and males of reproductive potential. It is not known whether these effects on fertility are reversible [see Adverse Reactions (6.1), Clinical Pharmacology (12.2)].

Animal Data

Oliceridine administered intravenously for 14 days prior to cohabitation and administered through GD15 caused prolonged estrous cycle lengths and decreased the number of implantations and viable embryos in female rats at doses producing plasma exposures ≥ 3 times the MRHD on an AUC basis [see Nonclinical Toxicology (13.1)].

8.4 Pediatric Use

The safety and effectiveness of OLINVYK in pediatric patients has not been established.

8.5 Geriatric Use

Controlled clinical studies of OLINVYK did not include sufficient numbers of subjects aged 65 and over to determine whether they respond differently from younger subjects. Other reported clinical experience has not identified differences in responses between the elderly and younger patients. In general, dose selection for an elderly patient should be cautious, usually starting at the low end of the dosing range, reflecting the greater frequency of decreased hepatic, renal, or cardiac function, and of concomitant disease or other drug therapy.

Elderly patients (aged 65 years or older) may have increased sensitivity to OLINVYK. In general, use caution when selecting a dosage for an elderly patient, usually starting at the low end of the dosing range, reflecting the greater frequency of decreased hepatic, renal, or cardiac function and of concomitant disease or other drug therapy.

Respiratory depression is the chief risk for elderly patients treated with opioids, and has occurred after large initial doses were administered to patients who were not opioid-tolerant or when opioids were co-administered with other agents that depress respiration. Titrate the dosage of OLINVYK slowly in geriatric patients and monitor for signs of central nervous system and respiratory depression [see Warnings and Precautions (5.8)].

8.6 Renal Impairment

In patients with end-stage renal disease, there was no clinically significant change in oliceridine clearance. Therefore, dosage adjustment of OLINVYK in patients with renal impairment is not required [see Clinical Pharmacology (12.3)].

8.7 Hepatic Impairment

In patients with mild or moderate hepatic impairment, no adjustment of the initial dose is needed; however, these patients may require less frequent dosing. When using OLINVYK in patients with severe hepatic impairment, consider reducing the initial dose, and administer subsequent doses only after a careful review of the patient’s severity of pain and overall clinical status [see Clinical Pharmacology (12.3)].

8.8 Poor Metabolizers of CYP2D6 Substrates

In patients who are known or suspected to be poor CYP2D6 metabolizers, based on genotype or previous history/experience with other CYP2D6 substrates, less frequent dosing of OLINVYK may be required. These patients should be closely monitored, and subsequent doses should be based on the patient’s severity of pain and response to treatment. [See Warnings and Precautions (5.6); Clinical Pharmacology (12.5)].

9 DRUG ABUSE AND DEPENDENCE

9.1 Controlled Substance

OLINVYK contains oliceridine, a Schedule II controlled substance.

9.2 Abuse

OLINVYK contains oliceridine, a substance with high potential for misuse and abuse, which can lead to the development of substance use disorder, including addiction [see Warnings and Precautions (5.1)].

Misuse is the intentional use, for therapeutic purposes, of a drug by an individual in a way other than prescribed by a healthcare provider or for whom it was not prescribed.

Abuse is the intentional, non-therapeutic use of a drug, even once, for its desirable psychological or physiological effects.

Drug addiction is a cluster of behavioral, cognitive, and physiological phenomena that may include a strong desire to take the drug, difficulties in controlling drug use (e.g., continuing drug use despite harmful consequences, giving a higher priority to drug use than other activities and obligations), and possible tolerance or physical dependence.

Misuse and abuse of OLINVYK increases risk of overdose, which may lead to central nervous system and respiratory depression, hypotension, seizures, and death. The risk is increased with concurrent abuse of OLINVYK with alcohol and/or other CNS depressants. Abuse of and addiction to opioids in some individuals may not be accompanied by concurrent tolerance and symptoms of physical dependence. In addition, abuse of opioids can occur in the absence of addiction.

All patients treated with opioids require careful and frequent reevaluation for signs of misuse, abuse, and addiction, because use of opioid analgesic products carries the risk of addiction even under appropriate medical use. Patients at high risk of OLINVYK abuse include those with a history of prolonged use of any opioid, including products containing oliceridine, those with a history of drug or alcohol abuse, or those who use OLINVYK in combination with other abused drugs.

“Drug-seeking” behavior is very common in persons with substance use disorders. Drug-seeking tactics include emergency calls or visits near the end of office hours, refusal to undergo appropriate examination, testing, or referral, repeated “loss” of prescriptions, tampering with prescriptions, and reluctance to provide prior medical records or contact information for other treating healthcare provider(s). “Doctor shopping” (visiting multiple prescribers to obtain additional prescriptions) is common among people who abuse drugs and people with substance use disorder. Preoccupation with achieving adequate pain relief can be appropriate behavior in a patient with inadequate pain control.

OLINVYK, like other opioids, can be diverted for nonmedical use into illicit channels of distribution. Careful record-keeping of prescribing information, including quantity, frequency, and renewal requests, as required by state and federal law, is strongly advised.

Proper assessment of the patient, proper prescribing practices, periodic reevaluation of therapy, and proper dispensing and storage are appropriate measures that help to limit abuse of opioid drugs.

Risk Specific to Abuse of OLINVYK

Abuse of OLINVYK injection poses a risk of overdose and death. The risk is increased with concurrent use of OLINVYK with alcohol and/or other CNS depressants.

Parenteral drug abuse is commonly associated with transmission of infectious diseases such as hepatitis and HIV.

9.3 Dependence

Both tolerance and physical dependence can develop during use of opioid therapy.

Tolerance is a physiological state characterized by a reduced response to a drug after repeated administration (i.e., a higher dose of a drug is required to produce the same effect that was once obtained at a lower dose).

Physical dependence is a state that develops as a result of physiological adaptation in response to repeated drug use, manifested by withdrawal signs and symptoms after abrupt discontinuation or a significant dose reduction of a drug.

Withdrawal may be precipitated through the administration of drugs with opioid antagonist activity (e.g., naloxone, nalmefene), mixed agonist/antagonist analgesics (e.g., pentazocine, butorphanol, nalbuphine), or partial agonists (e.g., buprenorphine). Physical dependence may not occur to a clinically significant degree until after several days to weeks of continued use.

Do not rapidly reduce or abruptly discontinue in a patient physically-dependent on opioids [see Dosage and Administration (2.4)]. If OLINVYK is abruptly discontinued in a physically-dependent patient, a withdrawal syndrome may occur, typically characterized by restlessness, lacrimation, rhinorrhea, perspiration, chills, myalgia, and mydriasis. Other signs and symptoms also may develop, including irritability, anxiety, backache, joint pain, weakness, abdominal cramps, insomnia, nausea, anorexia, vomiting, diarrhea, or increased blood pressure, respiratory rate, or heart rate.

Infants born to mothers physically dependent on opioids will also be physically dependent and may exhibit respiratory difficulties and withdrawal signs [see Use in Specific Populations (8.1)].

10 OVERDOSAGE

Clinical Presentation

Acute overdose with OLINVYK can be manifested by respiratory depression, somnolence progressing to stupor or coma, skeletal muscle flaccidity, cold and clammy skin, constricted pupils, and, in some cases, pulmonary edema, bradycardia, hypotension, hypoglycemia, partial or complete airway obstruction, atypical snoring, and death. Marked mydriasis rather than miosis may be seen due to severe hypoxia in overdose situations [see Clinical Pharmacology (12.2)]. Toxic leukoencephalopathy has been reported after opioid overdose and can present hours, days, or weeks after apparent recovery from the initial intoxication.

Treatment of Overdose

In case of overdose, priorities are the reestablishment of a patent and protected airway and institution of assisted or controlled ventilation, if needed. Employ other supportive measures (including oxygen and vasopressors) in the management of circulatory shock and pulmonary edema as indicated. Cardiac arrest or arrhythmias will require advanced life-support measures.

While naloxone reversal of OLINVYK’s effects has not been established in humans, some pharmacological effects (analgesia) of oliceridine have been shown to be reversed by naloxone in animals [see Clinical Pharmacology (12.2)]. For clinically significant respiratory or circulatory depression secondary to oliceridine overdose, administer an opioid overdose reversal agent such as naloxone or nalmefene.

Because the duration of opioid reversal is expected to be less than the duration of oliceridine in OLINVYK injection, carefully monitor the patient until spontaneous respiration is reliably reestablished. If the response to an opioid overdose reversal agent is suboptimal or only brief in nature, administer additional reversal agent as directed by the product’s prescribing information.

In an individual physically dependent on opioids, administration of the recommended usual dosage of the opioid overdose reversal agent will precipitate an acute withdrawal syndrome. The severity of the withdrawal symptoms experienced will depend on the degree of physical dependence and the dose of the reversal agent administered. If a decision is made to treat serious respiratory depression in the physically dependent patient, administration of the reversal agent should be initiated with care and by titration with smaller than usual doses of the reversal agent.

11 DESCRIPTION

The active ingredient in OLINVYK is oliceridine, an opioid agonist. Oliceridine fumarate is a white to lightly-colored solid that is sparingly soluble in water. The chemical name for oliceridine fumarate is [(3-methoxythiophen-2-yl)methyl]({2-[(9R)-9-(pyridin-2-yl)-6-oxaspiro[4.5]decan-9-yl]ethyl})amine fumarate, and the molecular formula is C22H30N2O2S·C4H4O4. The theoretical average molecular mass is 502.62 (fumarate salt) and 386.55 (free base). The structural formula of oliceridine fumarate is:

OLINVYK (oliceridine) injection is a clear, colorless, sterile, preservative-free solution, pH 6.4 to 7.4, in a glass vial for intravenous use.

Each milliliter of the solution contains 1.0 mg of oliceridine free base (1.3 mg of oliceridine fumarate salt), as well as L-histidine and mannitol, in water for injection.

12 CLINICAL PHARMACOLOGY

12.1 Mechanism of Action

Oliceridine is a full opioid agonist and is relatively selective for the mu-opioid receptor. The principal therapeutic action of oliceridine is analgesia. Like all full opioid agonists, there is no ceiling effect to analgesia for oliceridine. Clinically, dosage is titrated to provide adequate analgesia and may be limited by adverse reactions, including respiratory, and CNS depression.

The precise mechanism of the analgesic action is unknown. However, specific CNS opioid receptors for endogenous compounds with opioid-like activity have been identified throughout the brain and spinal cord and are thought to play a role in the analgesic effects of this drug.

12.2 Pharmacodynamics

In nonclinical models, the antinociceptive effect of oliceridine can be antagonized by the opioid antagonist naloxone.

Effects on the Central Nervous System

Opioids produces respiratory depression by direct action on brain stem respiratory centers. The respiratory depression involves a reduction in the responsiveness of the brain stem respiratory centers to both increases in carbon dioxide tension and electrical stimulation.

Opioids causes miosis, even in total darkness. Pinpoint pupils are a sign of opioid overdose but are not pathognomonic (e.g., pontine lesions of hemorrhagic or ischemic origins may produce similar findings). Marked mydriasis rather than miosis may be seen due to hypoxia in overdose situations.

Effects on the Gastrointestinal Tract and Other Smooth Muscle

Opioids causes a reduction in motility associated with an increase in smooth muscle tone in the antrum of the stomach and duodenum. Digestion of food in the small intestine is delayed and propulsive contractions are decreased. Propulsive peristaltic waves in the colon are decreased, while tone may be increased to the point of spasm, resulting in constipation. Other opioid-induced effects may include a reduction in biliary and pancreatic secretions, spasm of sphincter of Oddi, transient elevations in serum amylase, and opioid-induced esophageal dysfunction (OIED).

Effects on the Cardiovascular System

Opioids produces peripheral vasodilation, which may result in orthostatic hypotension or syncope. Manifestations of histamine release and/or peripheral vasodilation may include pruritus, flushing, red eyes, sweating, and/or orthostatic hypotension.

Effects on the Endocrine System

Opioids inhibit the secretion of adrenocorticotropic hormone (ACTH), cortisol, and luteinizing hormone (LH) in humans [see Adverse Reactions (6.1)]. They also stimulate prolactin, growth hormone (GH) secretion, and pancreatic secretion of insulin and glucagon.

Use of opioids for an extended period of time may influence the hypothalamic-pituitary-gonadal axis, leading to androgen deficiency that may manifest as low libido, impotence, erectile dysfunction, amenorrhea, or infertility. The causal role of opioids in the clinical syndrome of hypogonadism is unknown because the various medical, physical, lifestyle, and psychological stressors that may influence gonadal hormone levels have not been adequately controlled for in studies conducted to date [see Adverse Reactions (6.1)].

Effects on the Immune System

Opioids have been shown to have a variety of effects on components of the immune system in in vitro and animal models. The clinical significance of these findings is unknown. Overall, the effects of opioids appear to be modestly immunosuppressive.

Concentration-Analgesia Relationships

In a fixed-dose bunionectomy trial (N=192), the onset of action of OLINVYK (as measured by the two-stopwatch method) was almost immediate (median 1-3 minutes) upon administration of the first dose. Perceptible pain relief was achieved in the majority of patients within 5 minutes after the first dose of OLINVYK.

The minimum effective analgesic concentration will vary widely among patients, especially among patients who have been previously treated with opioid agonists. The minimum effective analgesic concentration of oliceridine for any individual patient may increase over time due to an increase in pain, the development of a new pain syndrome, and/or the development of analgesic tolerance [see Dosage and Administration (2.1, 2.3)].

Concentration-Adverse Experience Relationships

There is a general relationship between increasing oliceridine doses and increasing frequency of dose-related opioid adverse reactions such as nausea, vomiting, CNS effects, and respiratory depression. In opioid-tolerant patients, the situation may be altered by the development of tolerance to opioid-related adverse reactions [see Dosage and Administration (2.1, 2.2, 2.3)].

Cardiac Electrophysiology

The effect of oliceridine on the QTc interval was evaluated in 2 dedicated Thorough QT/QTc studies. A single-dose, randomized, positive- (moxifloxacin) and placebo-controlled 4 period crossover study evaluated the ECG effects of oliceridine at a therapeutic (3 mg IV infusion) and a supratherapeutic (6 mg IV infusion) dose in 62 healthy volunteers. Dose-dependent QTc prolongation (3 mg: 7 ms [upper 90% CI: 9 ms]; 6 mg: 12 ms [14 ms]), which occurred after peak oliceridine plasma concentration, was observed in this study.

A multi-dose, randomized, positive- (moxifloxacin) and placebo-controlled 3-way crossover study in 65 healthy volunteers evaluated intermittent dosing over 24 hours to the maximum daily cumulative dose of 27 mg. The maximum mean ΔΔQTcI was 11.7 ms (two-sided 90% UCI 14.7 ms) at 9 hours. Thereafter, the QTc effect did not progressively increase with repeat dosing, and despite continued dosing began to diminish after 12 hours.

The underlying mechanism and clinical significance of the transient QT changes seen in the single-dose and multiple-dose studies in healthy volunteers are unknown. These findings should be carefully considered when OLINVYK is administered in clinical settings where prolongation of the QT interval has been observed either due to the use of concomitant medications known to prolong the QT interval or to underlying medical conditions associated with QT interval prolongation.

12.3 Pharmacokinetics

Distribution

The mean steady-state volume of distribution of oliceridine ranges between 90-120 L indicating extensive tissue distribution. The plasma protein binding of oliceridine is 77%. In vitro data indicate that oliceridine is not an inhibitor of any of the major transporters, including breast cancer resistance protein (BCRP) and MDR1, at clinically relevant concentrations.

Elimination

Metabolism

In vitro studies suggest that oliceridine is metabolized primarily by CYP3A4 and CYP2D6 P450 hepatic enzymes, with minor contributions from CYP2C9 and CYP2C19 into inactive metabolites.

The mean clearance of oliceridine decreases slightly with increasing dose, resulting in greater-than-proportional exposure, particularly at doses greater than 2 mg. The percent of unchanged oliceridine excreted in the urine is low (0.97-6.75% of dose), reflecting its low renal clearance. The pharmacokinetics of oliceridine were not changed substantially (except for peak concentrations) when administered over different infusion times.

Excretion

Metabolic clearance is the major route of elimination of oliceridine, primarily by oxidation with subsequent glucuronidation. Additional biotransformation pathways included N−dealkylation, glucuronidation, and dehydrogenation. The majority of the metabolites (approximately 70%) are eliminated in the urine, with the remainder eliminated in the feces. Only a small amount of unchanged drug (0.97-6.75% of a dose) is found in the urine. The half-life of these metabolites (~44 hours) is much longer than that of unchanged oliceridine (1.3-3 hours). In vitro binding studies have demonstrated that none of these metabolites has any appreciable activity at the mu-opioid receptor.

Specific Populations

Renal Impairment

In a study comparing subjects with end stage renal disease (N=8) to healthy age and sex−matched healthy subjects (N=8), no significant difference in oliceridine clearance was observed. OLINVYK doses do not need to be adjusted in patients with renal impairment.

Hepatic Impairment

In a study of mild (N=8), moderate (N=8), or severe hepatic impairment (N=6), both clearance and total exposure were similar to age and sex-matched healthy controls (N=8). The mean half-life of oliceridine was increased in subjects with moderate (4.3 hours) or severe (5.8 hours) hepatic impairment, as compared with healthy subjects (2.1 hours), or patients with mild hepatic impairment (2.6 hours). The estimated volume of distribution of oliceridine was significantly higher in subjects with moderate or severe hepatic impairment (212 and 348 L, respectively), as compared to healthy subjects (126 L) or patients with mild hepatic impairment (167 L).

Based on these data, the initial dose of OLINVYK does not need to be reduced in patients with mild or moderate hepatic impairment, but these patients may require less frequent dosing. Use caution when dosing OLINVYK in patients with severe hepatic impairment. Consider reducing the initial dose, and administer subsequent doses only after a careful review of the patient’s severity of pain and overall clinical status.

Drug Interaction Studies

In vitro studies suggest that oliceridine is metabolized primarily by the CYP3A4 and CYP2D6 P450 hepatic enzymes, with minor contributions from CYP2C9 and CYP2C19. Inhibition studies using selective inhibitors of all the major CYP enzymes show that only the inhibition of CYP3A4 and CYP2D6 significantly affects the metabolism of oliceridine in these assays, suggesting that the contribution of CYP2C9 and CYP2C19 to the metabolism of oliceridine is minor.

The effect of concomitant administration of a CYP2D6 inhibitor on the pharmacokinetics of OLINVYK, although not studied, may be similar to that noted in subjects who are CYP2D6 poor metabolizers. The plasma clearance of oliceridine in CYP2D6 poor metabolizers is approximately 50% of plasma clearance in subjects who are nonpoor CYP2D6 metabolizers [See Pharmacogenomics (12.5)].

In healthy subjects CYP2D6 poor metabolizers (n=4) given a single 0.25 mg dose of OLINVYK after 5 days of itraconazole 200 mg QD (a strong CYP3A4 inhibitor), the total exposure (AUC) of OLINVYK was increased by approximately 80%; however, the peak concentration was not significantly affected [See Pharmacogenomics (12.5)]. The mean clearance of oliceridine was reduced to approximately 30% of that observed in nonpoor metabolizers of CYP2D6 [see Drug Interactions (7)].

Oliceridine does not inhibit any P450 enzymes at clinically relevant concentrations.

12.5 Pharmacogenomics

Oliceridine is metabolized by polymorphic enzyme CYP2D6. CYP2D6 poor metabolizers have little to no enzyme activity. Approximately 3 to 10% of Whites, 2 to 7% of African Americans, and <2% of Asians, generally lack the capacity to metabolize CYP2D6 substrates and are classified as poor metabolizers.

In healthy subjects who are CYP2D6 poor metabolizers, the AUC0−inf of oliceridine was approximately 2-fold higher than in subjects who are nonpoor CYP2D6 metabolizers. [see Warnings and Precautions (5.6); Use in Specific Populations (8.8)].

13 NONCLINICAL TOXICOLOGY

13.1 Carcinogenesis, Mutagenesis, Impairment of Fertility

Carcinogenesis:

Long-term animal studies have not been completed to evaluate the carcinogenic potential of oliceridine.

Mutagenesis:

Oliceridine was negative in an in vitro Ames bacterial reverse mutation assay, the in vitro chromosomal aberration assay using human peripheral blood lymphocytes, and the in vivo rat micronucleus assay.

Impairment of Fertility:

In a fertility and early embryonic development study, oliceridine administered to female rats via continuous intravenous infusion at 6, 12, or 24 mg/kg/day for 14 days prior to cohabitation and through GD 15 for a total of 29-42 days resulted in prolonged estrous cycle lengths and decreased number of implantations and viable embryos at doses ≥12 mg/kg/day (≥3 times the estimated plasma exposure at the MRHD of 27 mg/day on an AUC basis).

Oliceridine did not alter male fertility at any dose tested. Males were dosed at 6, 12, or 24 mg/kg/day, producing plasma exposures up to 8 times the estimated plasma exposure at the MRHD, for 28 days prior to cohabitation, throughout the mating period and up to the time of scheduled necropsy for a total of 64-65 days of dosing.

13.2 Animal Toxicology and/or Pharmacology

Continuous intravenous infusion of oliceridine to rats for 14 days followed by one-day withdrawal from the treatment resulted in opioid withdrawal stress-related gastric lesions including erosions/ulcers in the glandular stomach, mucosal congestion/hemorrhage and degeneration/necrosis in the nonglandular stomach at all doses tested including the low dose producing plasma exposure 2 times the estimated human exposure at the MRHD on an AUC basis. The effect is believed to be due to acute withdrawal stress, as similar findings were not noted in rats sacrificed immediately after the last dose of oliceridine.

14 CLINICAL STUDIES

The efficacy of OLINVYK was established in two randomized, double-blind, placebo- and morphine-controlled studies of patients with moderate to severe acute pain following orthopedic surgery-bunionectomy or plastic surgery-abdominoplasty. In each study, pain intensity was measured using a patient-reported numeric rating scale (11-point numerical scale ranging from 0-10, where zero corresponds to no pain and 10 corresponds to worst pain imaginable).

In each study, patients were randomized to one of three OLINVYK treatment regimens, a placebo-control regimen, or a morphine-control regimen. Each blinded treatment regimen consisted of a loading dose, incremental doses delivered as needed via patient-controlled analgesia (PCA) device, and supplemental doses, beginning 1 hour after the initial dose, and hourly thereafter, as needed. The loading dose for all OLINVYK treatment regimens was 1.5 mg; demand doses were 0.1, 0.35 or 0.5 mg, according to the assigned treatment group; supplemental doses were 0.75 mg. The loading dose for the morphine treatment regimen was 4 mg; the demand dose was 1 mg; supplemental doses were 2 mg. The placebo-control regimen was volume-matched. A lockout interval of 6 minutes was used for all PCA regimens. For Studies 1 and 2, patients may have received rescue pain medication (pre-defined in the protocols as etodolac 200 mg every 6 hours, as needed) if the patient requested rescue pain medication and reported a Numeric Rating Scale score ≥4.

14.1 Study 1 – Orthopedic Surgery - Bunionectomy

A total of 389 patients (placebo n=79, OLINVYK 0.1 mg n=76, OLINVYK 0.35 mg n=79, OLINVYK 0.5 mg n=79, and morphine n=76), 19-74 years of age, with moderate to severe acute pain following orthopedic surgery-bunionectomy, were treated for up to 48 hours in Study 1 (NCT02815709). Treatment began after discontinuation of regional anesthesia in patients with pain intensity of ≥4 on a 0-10 numeric rating scale [NRS] within 9 hours after discontinuation of regional anesthesia. The analgesic effects were measured using the Summed Pain Intensity Differences over 48 hours (SPID-48). The SPID-48 is calculated by multiplying the Pain Intensity Difference (calculated by subtracting the pain intensity at a particular timepoint from the pain intensity at baseline) scores at each post-baseline timepoint by the duration (in hours) since the preceding timepoint, and then summing the values, over 48 hours. The majority of the study population was female (85%), and the mean age was 45 years. Patients were 69% White, 24% Black or African American, 4% Asian, 1% Native Hawaiian or Other Pacific Islander, 1% American Indian or Alaska Native and 1% other races. Twenty-five (25%) of patients were Hispanic or Latino.

The majority of patients treated with OLINVYK (0.1 mg treatment group: 83%; 0.35 mg treatment group 87%; 0.5 mg treatment group 84%) completed the randomized treatment period (compared to 60% of patients treated with placebo). Nine percent (9%), 4%, and 5% of patients in the 0.1 mg, 0.35 mg and 0.5 mg OLINVYK treatment groups, respectively, discontinued study medication due to lack of efficacy (compared to 34% of patients treated with placebo). In the 0.1 mg, 0.35 mg and 0.5 mg OLINVYK treatment groups, 41%, 20%, and 17% of patients, respectively, used the protocol-specified rescue medication etodolac, compared to 77% of patients treated with placebo.

The mean (SD) baseline pain intensity score was 6.7 (1.7). A statistically significantly greater analgesic effect was observed in both 0.35 mg and 0.5 mg OLINVYK treatment groups, compared to the placebo group (see Table 7). The mean pain intensities over time for placebo, 0.35 mg and 0.5 mg oliceridine and morphine treatment arms are shown in Figure 1.

Table 7: SPID-48 (Efficacy Endpoint) Results in Study 1 (Orthopedic Surgery - Bunionectomy)
Efficacy Measure | Placebo regimen (N=79) | OLINVYK |  | Morphine regimen (N=76)
Efficacy Measure | Placebo regimen (N=79) | 0.35 mg regimen (N=79) | 0.5 mg regimen (N=79) | Morphine regimen (N=76)
SPID-48
Average | 85 | 138 | 164 | 193
Differencea | --- | 47.5 | 80 | 105
95 % Confidence Interval |  | (19, 75) | (52, 108) | (77, 132)
a Treatments compared to placebo

Figure 1: Mean Pain Intensity versus Time Plot in Study 1

Note: Doses over the maximum recommended total cumulative daily dosage (27 mg) were treated as rescue medication in Figure 1. Pre-rescue pain scores were carried for 6 hours following the use of rescue medication.

In Study 1, 60% of patients in the OLINVYK 0.35 mg treatment group, and 63% of patients in the OLINVYK 0.5 mg treatment group reached the maximum recommended total cumulative daily dosage of 27 mg. The median (minimum) time to reach the 27 mg maximum recommended cumulative total daily dosage was 15.8 (9.1) hours for patients in the OLINVYK 0.35 mg treatment group, and 13.6 (6.8) hours for patients in the OLINVYK 0.5 mg treatment group.

14.2 Study 2 – Plastic Surgery - Abdominoplasty

A total of 401 patients (placebo n=81, OLINVYK 0.1 mg n=77, OLINVYK 0.35 mg n=80, OLINVYK 0.5 mg n=80, and morphine n=83), 20-71 years of age, with moderate to severe acute pain following plastic surgery-abdominoplasty, were treated for up to 24 hours in Study 2 (NCT02820324). The majority of the study population was female (99%), and the mean age was 41 years. Patients were 64% white, 31% Black or African American, 2% Asian, 1% Native Hawaiian or Other Pacific Islander, 0.2% American Indian or Alaska Native and 1% other races. Thirty-three (33%) of patients were Hispanic or Latino. Treatment began after discontinuation of general anesthesia in patients with NRS ≥5 within 4 hours after end of surgery. The analgesic effects were measured using the Summed Pain Intensity Differences over 24 hours (SPID-24).

The majority of patients treated with OLINVYK (0.1 mg treatment group: 86%; 0.35 mg treatment group: 90%; 0.5 mg treatment group: 87%) completed the randomized treatment period without discontinuing study medication (compared to 74% of patients treated with placebo). Eleven percent (11%), 3%, and 5% of patients in the OLINVYK 0.1 mg, 0.35 mg and 0.5 mg treatment groups, respectively, discontinued study medication due to lack of efficacy (compared to 22% of patients treated with placebo). In the OLINVYK 0.1 mg, 0.35 mg, and 0.5 mg treatment groups, 31%, 21%, and 18% of patients, respectively, used protocol-specified rescue medication etodolac, compared to 49% in patients treated with placebo.

The mean (SD) baseline pain intensity score was 7.3 (1.5). A statistically significantly greater analgesic effect was observed in the OLINVYK 0.5 mg and 0.35 mg treatment groups, compared to the placebo group (see Table 8). The analgesic effect was not significantly better in the OLINVYK 0.1 mg treatment group than in the placebo group. The mean pain intensities over time for placebo, 0.35 mg and 0.5 mg oliceridine and morphine treatment arms are shown in Figure 2.

Table 8: SPID-24 (Efficacy Endpoint) Results in Study 2 (Plastic Surgery-Abdominoplasty Study)
Efficacy Measure |  | OLINVYK
 | Placebo regimen; (N=81) | 0.35 mg regimen; (N=80) | 0.5 mg regimen; N=80) | Morphine regimen; (N=83)
SPID-24
Average | 75 | 90 | 94 | 103
Differencea | --- | 14 | 18 | 30
95 % Confidence Interval |  | (2, 26) | (5, 30) | (17, 42)
a Treatments compared to placebo

Figure 2: Mean Pain Intensity versus Time Plot in Study 2

Note: Doses over the maximum recommended total cumulative daily dosage (27 mg) were treated as rescue medication in Figure 2. Pre rescue pain scores were carried for 6 hours following use of rescue medication. In Study 2, 28% of patients in the 0.35 mg dose group, and 43% of patients in the 0.5 mg dose group, reached the maximum recommended 27 mg total cumulative daily dosage. The median (minimum) time to reach the 27 mg maximum recommended cumulative total daily dosage was 19.4 (8.3) hours for patients in the 0.35 mg dose group, and 14.1 (6.4) hours for patients in the 0.5 mg dose group.

16 HOW SUPPLIED/STORAGE AND HANDLING

OLINVYK (oliceridine) injection is a clear, colorless, preservative free solution for intravenous use supplied as follows:

NDC# 71308-011-10: 1 mg/mL, sterile solution in single-dose, 2 mL clear glass vials with gray stoppers topped with overseals with gray plastic flip-off caps (carton of 10 vials)

NDC# 71308-021-10: 2 mg/2 mL (1 mg/mL), sterile solution in single-dose, 2 mL clear glass vials with gray stoppers topped with overseals with orange plastic flip-off caps (carton of 10 vials)

NDC# 71308-301-10: 30 mg/30 mL (1 mg/mL), sterile solution in single-patient-use, 30 mL clear glass vials with gray stoppers topped with overseals with purple plastic flip-off caps (carton of 10 vials). For PCA Use Only.

Store at controlled room temperature 20°-25°C (68°-77°F); excursions permitted to 15°-30°C (59°-86°F) [see USP Controlled Room Temperature]. Protect from freezing. Protect from light.

17 PATIENT COUNSELING INFORMATION

Addiction, Abuse, and Misuse

Inform patients that the use of OLINVYK, even when taken as recommended, can result in addiction, abuse, and misuse, which can lead to overdose and death [see Warnings and Precautions (5.1)].

Life-Threatening Respiratory Depression

Inform patients of the risk of life-threatening respiratory depression, including information that the risk is greatest when starting OLINVYK or when the dosage is increased, and that it can occur even at recommended dosages.

Hyperalgesia and Allodynia

Advise patients to inform their healthcare provider if they experience symptoms of hyperalgesia, including worsening pain, increased sensitivity to pain, or new pain [see Warnings and Precautions (5.7); Adverse Reactions (6.2)].

Serotonin Syndrome

Inform patients that opioids could cause a rare but potentially life-threatening condition called serotonin syndrome resulting from concomitant administration of serotonergic drugs. Warn patients of the symptoms of serotonin syndrome and to seek medical attention right away if symptoms develop after discharge from the hospital. Instruct patients to inform their healthcare provider if they are taking or plan to take serotonergic medications [see Drug Interactions (7)].

Constipation

Advise patients of the potential for severe constipation, including management instructions and when to seek medical attention [see Adverse Reactions (6), Clinical Pharmacology (12.2)].

Distributed by:

Trevena, Inc.

Chesterbrook, PA 19087 USA

OLINVYK® is a trademark of Trevena, Inc.

© 2023 Trevena, Inc. All rights reserved.

OLI-005 12/2025

Principal Display Panel - Vial Label

NDC 71308-011-01

Olinvyk®
(oliceridine) injection

1 mg/mL Single-dose Vials. Discard unused portion. FOR INTRAVENOUS USE ONLY Rx only Sterile

Principal Display Panel - Carton Label

NDC 71308-011-10

Olinvyk®
(oliceridine) injection

10 x 1 mg/mL 1 mg/mL Single-dose Vials. Discard unused portion. FOR INTRAVENOUS USE ONLY Rx only Sterile

Principal Display Panel - Vial Label

NDC 71308-021-01

Olinvyk®
(oliceridine) injection

2 mg/2 mL (1 mg/mL) Single-dose Vials. Discard unused portion. FOR INTRAVENOUS USE ONLY Rx only Sterile

Principal Display Panel - Carton Label

NDC 71308-021-10

Olinvyk®
(oliceridine) injection

10 x 2 mg/2 mL 2 mg/2 mL (1 mg/mL) Single-dose Vials. Discard unused portion. FOR INTRAVENOUS USE ONLY Rx only Sterile

Principal Display Panel - Vial Label

NDC 71308-301-01 Rx only

Olinvyk®
(oliceridine) injection

30 mg/30 mL (1 mg/mL) Single-dose Vials. Discard unused portion. FOR INTRAVENOUS USE ONLY Rx only Sterile

Principal Display Panel - Carton Label

NDC 71308-301-10

Olinvyk®
(oliceridine) injection

10 x 30 mg/30 mL 30 mg/30 mL (1 mg/mL) Single-dose Vials. Discard unused portion. FOR INTRAVENOUS USE ONLY Rx only Sterile